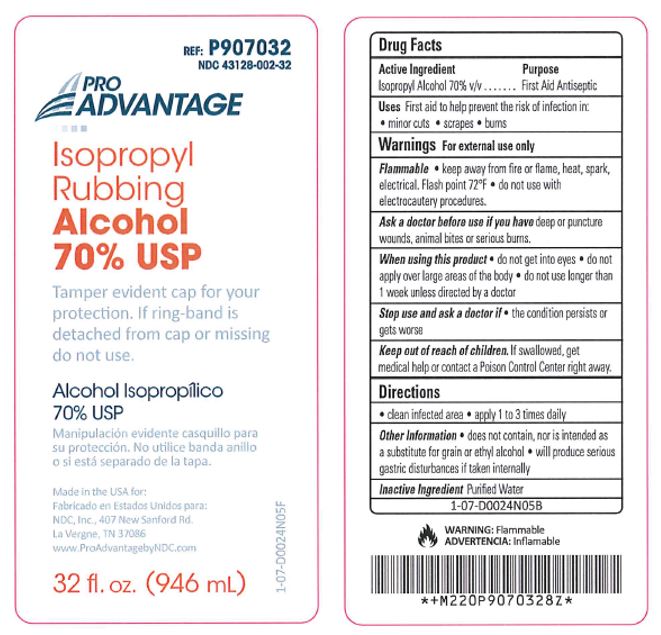 DRUG LABEL: Isopropyl Rubbing Alcohol
NDC: 43128-002 | Form: SOLUTION
Manufacturer: NDC, Inc.
Category: otc | Type: HUMAN OTC DRUG LABEL
Date: 20241115

ACTIVE INGREDIENTS: ISOPROPYL ALCOHOL 70 mL/100 mL
INACTIVE INGREDIENTS: WATER

Isopropyl Rubbing Alcohol

Drug Facts

Active Ingredient

Isopropyl Alcohol 70% v/v

Purpose

First Aid Antiseptic

Uses

First aid to help prevent the risk of infection in:

- minor cuts
- scrapes
- burns

WARNINGS

For external use only

Flammable

- keep away from fire or flame, heat, spark, electrical. Flash point 72°F
- do not use with electrocautery procedures.

Ask a doctor before use if you havedeep or puncture wounds, animal bites or serious burns.

When using this product

- do not get into eyes
- do not apply over large areas of the body
- do not use longer than 1 week unless directed by a doctor

Stop use and ask a doctor if

- the condition persists or gets worse

Keep out of reach of children.If swallowed, get medical help or contact a Poison Control Center right away.

Directions

- clean infected area
- apply 1 to 3 times daily

Other information

- does not contain, nor is intended as a substitute for grain or ethyl alcohol
- will produce serious gastric disturbances if taken internally

Inactive Ingredient

Purified Water

PRINCIPAL DISPLAY PANEL

REF: P907132

NDC 43128-002-32

Pro
ADVANTAGE®

Isopropyl Rubbing
Alcohol 70% USP

Tamper evident cap for your protection.
If ring-band is detached from cap or missing do not use.

WARNING:Flammable

Made in USA for:
NDC, Inc., 407 New Sanford Rd.
La Vergne, TN 37086
www.ProAdvantagebyNDC.com

32 fl. oz. (946 mL)